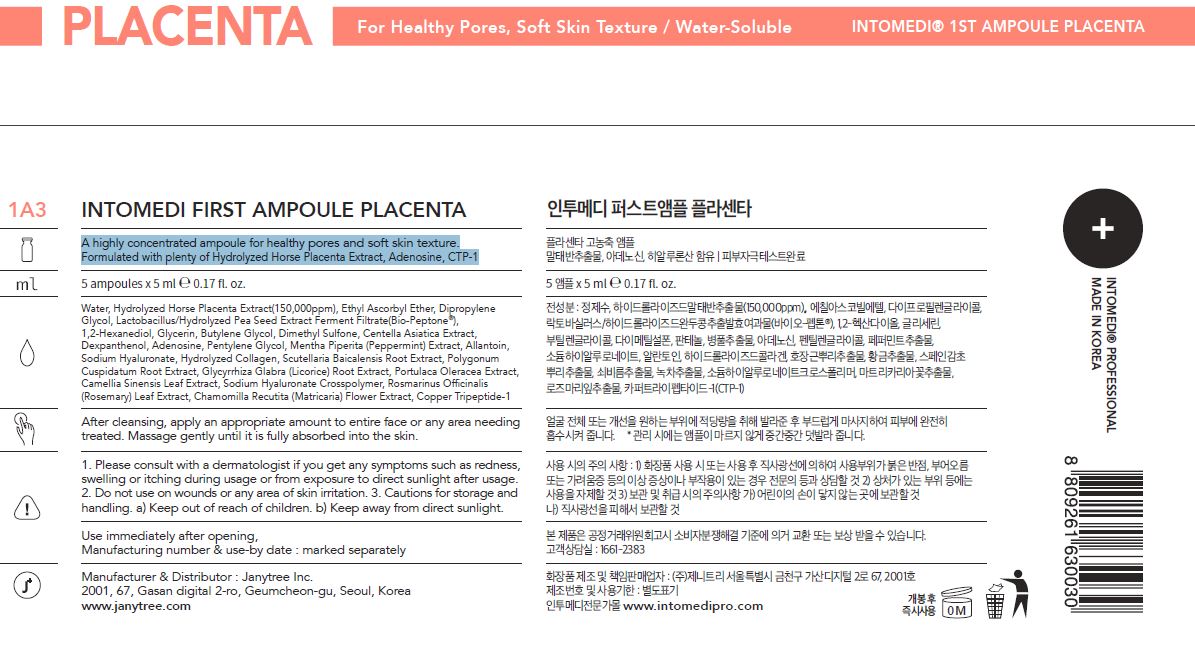 DRUG LABEL: INTOMEDI FIRST AMPOULE PLACENTA
NDC: 82879-0005 | Form: LIQUID
Manufacturer: Janytree Inc.
Category: otc | Type: HUMAN OTC DRUG LABEL
Date: 20220712

ACTIVE INGREDIENTS: ADENOSINE 0.1 g/100 mL
INACTIVE INGREDIENTS: BUTYLENE GLYCOL; WATER; GLYCERIN

INACTIVE INGREDIENTS

Water, Hydrolyzed Horse Placenta Extract(150,000ppm), Ethyl Ascorbyl Ether, Dipropylene
Glycol, Lactobacillus/Hydrolyzed Pea Seed Extract Ferment Filtrate(Bio-Peptone®),
1,2-Hexanediol, Glycerin, Butylene Glycol, Dimethyl Sulfone, Centella Asiatica Extract,
Dexpanthenol, Pentylene Glycol, Mentha Piperita (Peppermint) Extract, Allantoin,
Sodium Hyaluronate, Hydrolyzed Collagen, Scutellaria Baicalensis Root Extract, Polygonum
Cuspidatum Root Extract, Glycyrrhiza Glabra (Licorice) Root Extract, Portulaca Oleracea Extract,
Camellia Sinensis Leaf Extract, Sodium Hyaluronate Crosspolymer, Rosmarinus Officinalis
(Rosemary) Leaf Extract, Chamomilla Recutita (Matricaria) Flower Extract, Copper Tripeptide-1

ACTIVE INGREDIENTS

adenosine

PURPOSE

A highly concentrated ampoule for healthy pores and soft skin texture.
Formulated with plenty of Hydrolyzed Horse Placenta Extract, Adenosine, CTP-1

WARNINGS

For external use only When using this product
■ If following abnormal symptoms occurs after using the product, stop using the product and consult with a skin specialist. Symptoms : Red specks, swelling, itching
■ Do not use on the skin parts affected by wound, eczema, or dermatitis.
Keep out of reach of children.
■ If swallowed, get a medical help or contact a person in control center immediately.
■ Avoid contact with eyes.

KEEP OUT OF REACH OF CHILDREN

If swallowed, get a medical help or contact a person in control center immediately.

INDICATIONS AND USAGE

apply a proper amount to the skin, and massage gently until fully absorbed

DOSAGE AND ADMINISTRATION

for external use only